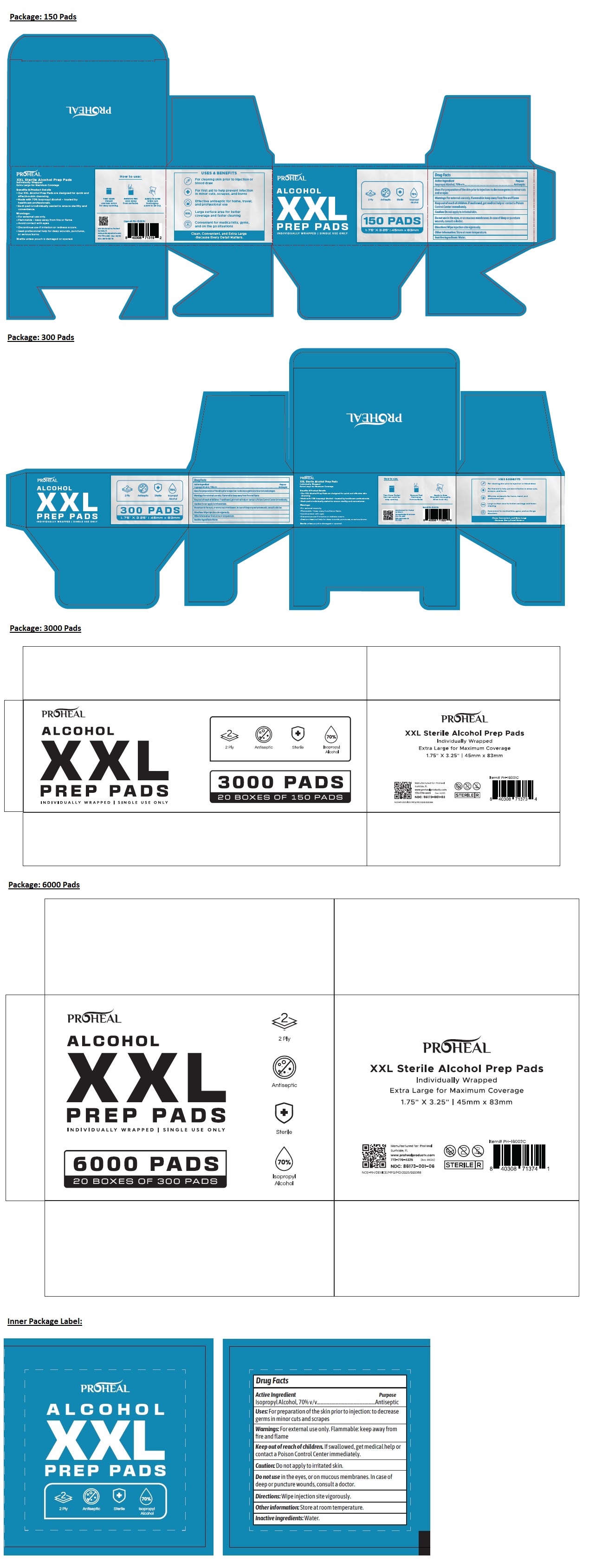 DRUG LABEL: PROHEAL ALCOHOL XXL PREP PADS
NDC: 86173-001 | Form: CLOTH
Manufacturer: Click Industries LLC
Category: otc | Type: HUMAN OTC DRUG LABEL
Date: 20251020

ACTIVE INGREDIENTS: ISOPROPYL ALCOHOL 70 mL/100 mL
INACTIVE INGREDIENTS: WATER

PROHEAL ALCOHOL XXL PREP PADS

Active Ingredient

Isopropyl Alcohol, 70% v/v

Purpose

Antiseptic

Uses:

For preparation of the skin prior to injection: to decrease germs in minor cuts and scrapes

Warnings:

For external use only. Flammable: keep away from fire and flame

Caution: Do not apply to irritated skin.

Do not use in the eyes, or on mucous membranes. In case of deep or puncture wounds, consult a doctor.

Keep out of reach of children. If swallowed, get medical help or contact a Poison Control Center immediately.

Directions:

Wipe injection site vigorously.

Other information:

Store at room temperature.

Inactive ingredients:

Water.

INDIVIDUALLY WRAPPED | SINGLE USE ONLY

2 Ply

Sterile

Extra Large for Maximum Coverage

Benefits & Product Details

- Our XXL Alcohol Prep Pads are designed for quick and effective skin cleansing.
- Made with 70% Isopropyl Alcohol - trusted by healthcare professionals.
- Each pad is individually sealed to ensure sterility and convenience.

• Discontinue use if irritation or redness occurs.

Sterile unless pouch is damaged or opened.

How to use:

Tea Open Packet
Use tear notch for easy opening.

Remove Pad
Hold away from surfaces.

Apply to Area
Wipe skin thoroughly.
Allow to air dry.

Manufactured for: ProHeal Surfside, FL
www.prohealproducts.com
772-776-4325 (Rev. 08/25)

USES & BENEFITS

For cleaning skin prior to injection or blood draw

For first aid to help prevent infection in minor cuts, scrapes, and burns

Effective antiseptic for home, travel and professional use

Large surface are for better coverage and faster cleaning

Convenient for medical kits, gyms, and on the go situations

Clean, Convenient, and Extra Large
-Because Every Detail Matters.